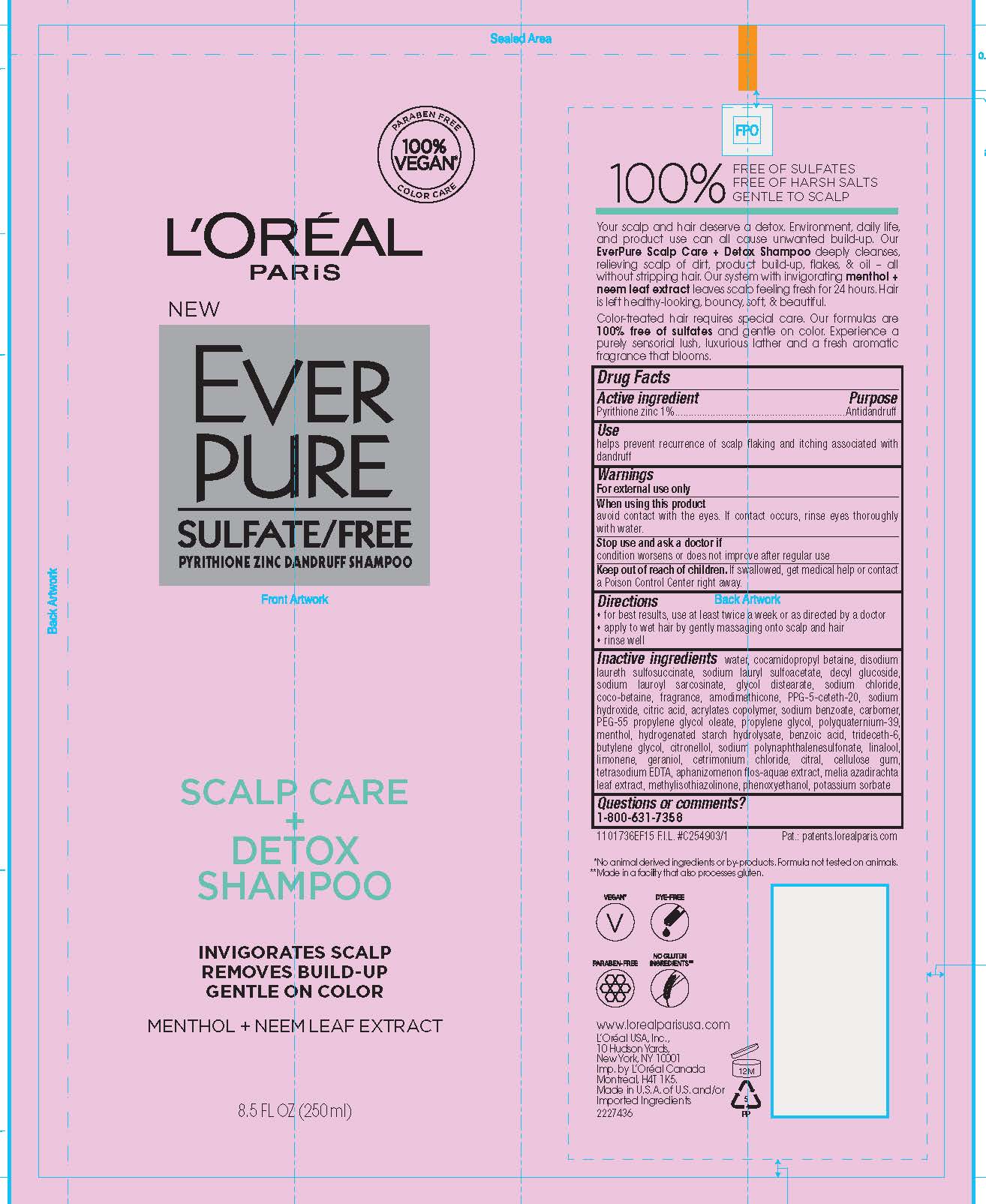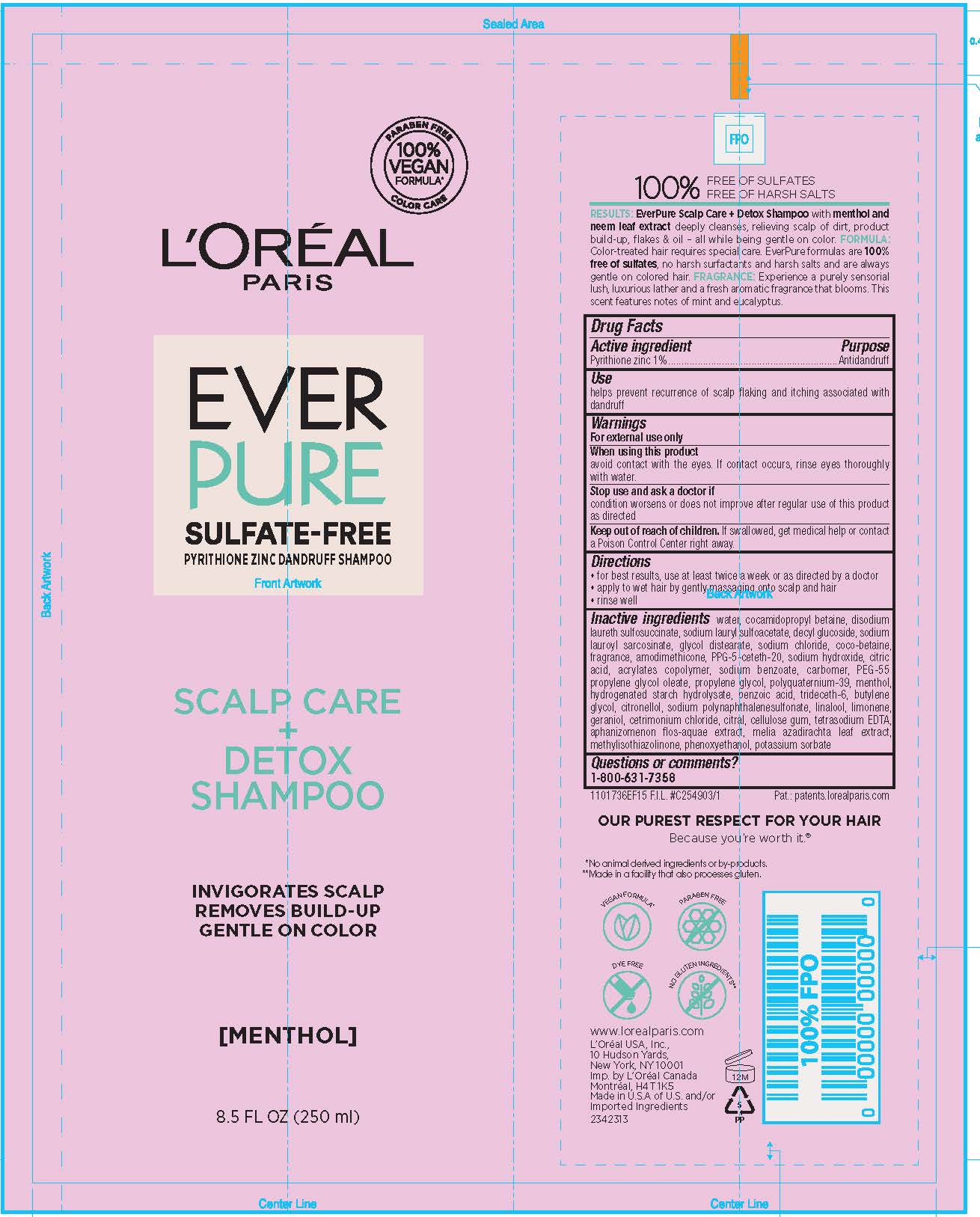 DRUG LABEL: LOreal Paris Ever Pure Dandruff Scalp Care and Detox
NDC: 49967-056 | Form: SHAMPOO
Manufacturer: L'Oreal USA Products Inc
Category: otc | Type: HUMAN OTC DRUG LABEL
Date: 20231211

ACTIVE INGREDIENTS: PYRITHIONE ZINC 10 mg/1 mL
INACTIVE INGREDIENTS: WATER; COCAMIDOPROPYL BETAINE; DISODIUM LAURETH SULFOSUCCINATE; SODIUM LAURYL SULFOACETATE; DECYL GLUCOSIDE; SODIUM LAUROYL SARCOSINATE; GLYCOL DISTEARATE; SODIUM CHLORIDE; COCO-BETAINE; AMODIMETHICONE (1300 CST); PPG-5-CETETH-20; SODIUM HYDROXIDE; CITRIC ACID MONOHYDRATE; SODIUM BENZOATE; CARBOMER 940; PROPYLENE GLYCOL; POLYQUATERNIUM-39 (22.5/51/26.5 ACRYLIC ACID/ACRYLAMIDE/DADMAC; 1600000 MW); MENTHOL; HYDROGENATED STARCH HYDROLYSATE; BENZOIC ACID; TRIDECETH-6; BUTYLENE GLYCOL; .BETA.-CITRONELLOL, (R)-; LINALOOL, (+/-)-; LIMONENE, (+)-; GERANIOL; CETRIMONIUM CHLORIDE; CITRAL; CARBOXYMETHYLCELLULOSE SODIUM (0.7 CARBOXYMETHYL SUBSTITUTION PER SACCHARIDE; 150 MPA.S AT 1%); EDETATE SODIUM; APHANIZOMENON FLOSAQUAE; AZADIRACHTA INDICA LEAF; METHYLISOTHIAZOLINONE; PHENOXYETHANOL; POTASSIUM SORBATE

Drug Facts

Active ingredient

Pyrithone zinc 1%

Purpose

Antidandruff

Use

helpls prevent recurrence of scalp flaking and itching associated with dandruff

Warnings

For external use only

When using this product

avoid contact with the eyes. If contact occurs, rinse eyes thoroughly with water.

Stop use and ask a doctor if

condition worsens or does not improve after regular use

Keep out of reach of children.

If swallowed, get medical help or contact a Poison Control Center right away.

Directions

- for best results, use at least twice a week or as directed by a doctor
- apply to wet hair by gently massaging onto scalp and hair
- rinse well

Inactive ingredients

water, cocamidopropyl betaine, disodium laureth sulfosuccinate, sodium lauryl sulfoacetate, decyl glucoside, sodium lauroyl sarcosinate, glycol distearate, sodium chloride, coco-betaine, fragrance, amodimethicone, PPG-5-ceteth-20, acrylates copolymer, sodium benzoate, carbomer, PEG-55 propylene glycol oleate, propylene glycol, polyquaternium-39, menthol, hydrogenated starch hydrolysate, benzoic acid, trideceth-6, butylene glycol, citronellol, sodium polynaphthalenesulfonate, linalool, limonene, geraniol, cetrimonium chloride, citral, cellulose gum, tetrasodum EDTA, aphanizomenon flos-aquae extract, melia azadirachta leaf extract, methylisothiazolinone, phenoxyethanol, potassium sorbate

Questions or comments?

1-800-631-7358